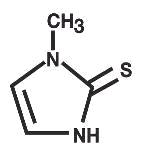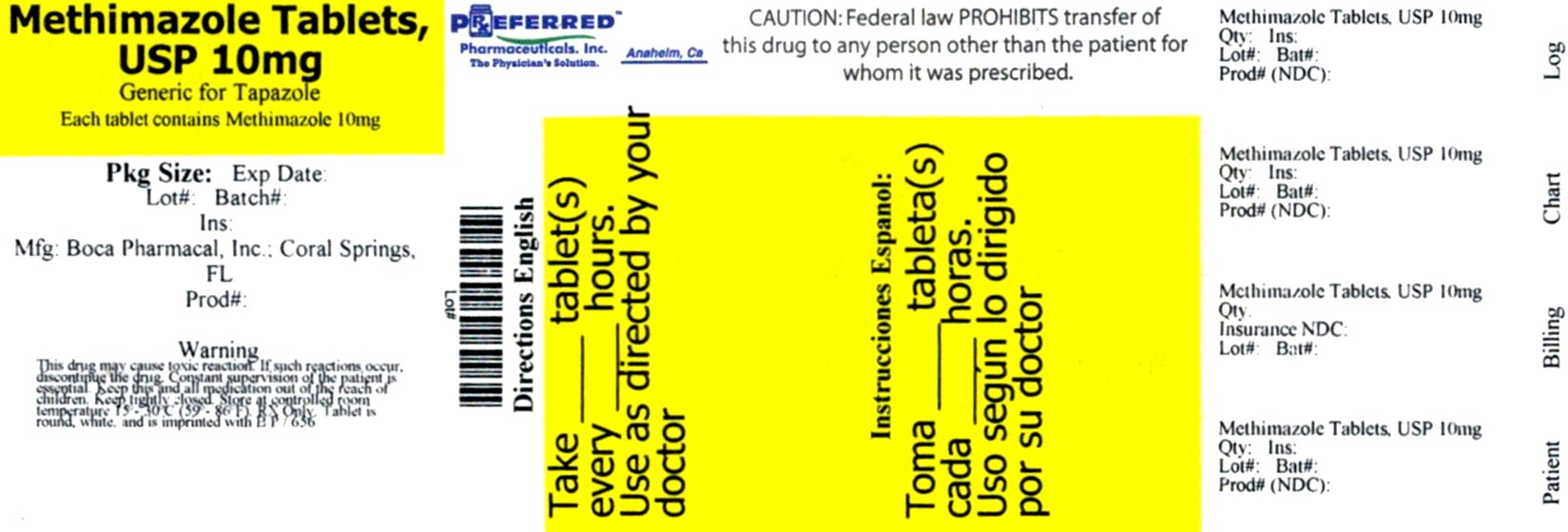 DRUG LABEL: METHIMAZOLE
NDC: 68788-0681 | Form: TABLET
Manufacturer: Preferred Pharmaceuticals, Inc.
Category: prescription | Type: HUMAN PRESCRIPTION DRUG LABEL
Date: 20161216

ACTIVE INGREDIENTS: METHIMAZOLE 10 mg/1 1
INACTIVE INGREDIENTS: LACTOSE MONOHYDRATE; STARCH, CORN; MAGNESIUM STEARATE

METHIMAZOLE Tablets, USP
Rx Only

DESCRIPTION

Methimazole (1-methylimidazole-2-thiol) is a white, crystalline substance that is freely soluble in water. It differs chemically from the drugs of the thiouracil series primarily because it has a 5- instead of a 6-membered ring.

Each tablet contains 5 or 10 mg (43.8 or 87.6 µmol) methimazole, an orally administered antithyroid drug. Each tablet also contains lactose monohydrate, magnesium stearate and pregelatinized starch.

The molecular weight is 114.17, and the molecular formula is C4H6N2S. The structural formula is as follows:

CLINICAL PHARMACOLOGY

Methimazole inhibits the synthesis of thyroid hormones and thus is effective in the treatment of hyperthyroidism. The drug does not inactivate existing thyroxine and triiodothyronine that are stored in the thyroid or circulating in the blood nor does it interfere with the effectiveness of thyroid hormones given by mouth or by injection.

The actions and use of methimazole are similar to those of propylthiouracil. On a weight basis, the drug is at least 10 times as potent as propylthiouracil, but methimazole may be less consistent in action.

Methimazole is readily absorbed from the gastrointestinal tract. It is metabolized rapidly and requires frequent administration.

Methimazole is excreted in the urine.

In laboratory animals, various regimens that continuously suppress thyroid function and thereby increase TSH secretion result in thyroid tissue hypertrophy. Under such conditions, the appearance of thyroid and pituitary neoplasms has also been reported.

Regimens that have been studied in this regard include antithyroid agents as well as dietary iodine deficiency, subtotal thyroidectomy, implantation of autonomous thyrotropic hormone-secreting pituitary tumors, and administration of chemical goitrogens.

INDICATIONS AND USAGE

Methimazole is indicated in the medical treatment of hyperthyroidism. Long-term therapy may lead to remission of the disease.

Methimazole may be used to ameliorate hyperthyroidism in preparation for subtotal thyroidectomy or radioactive iodine therapy.

Methimazole is also used when thyroidectomy is contraindicated or not advisable.

CONTRAINDICATIONS

Methimazole is contraindicated in the presence of hypersensitivity to the drug and in nursing mothers because the drug is excreted in milk.

WARNINGS

Agranulocytosis is potentially a serious side effect. Patients should be instructed to report to their physicians any symptoms of agranulocytosis, such as fever or sore throat. Leukopenia, thrombocytopenia, and aplastic anemia (pancytopenia) may also occur. The drug should be discontinued in the presence of agranulocytosis, aplastic anemia (pancytopenia), hepatitis, or exfoliative dermatitis. The patient’s bone marrow function should be monitored.

Due to the similar hepatic toxicity profiles of methimazole and propylthiouracil, attention is drawn to the severe hepatic reactions which have occurred with both drugs. There have been rare reports of fulminant hepatitis, hepatic necrosis, encephalopathy, and death.

Symptoms suggestive of hepatic dysfunction (anorexia, pruritus, right upper quadrant pain, etc.) should prompt evaluation of liver function. Drug treatment should be discontinued promptly in the event of clinically significant evidence of liver abnormality including hepatic transaminase values exceeding 3 times the upper limit of normal.

Methimazole can cause fetal harm when administered to a pregnant woman. Methimazole readily crosses the placental membranes and can induce goiter and even cretinism in the developing fetus. In addition, rare instances of congenital defects: aplasia cutis, as manifested by scalp defects; esophageal atresia with tracheoesophageal fistula; and choanal atresia with absent/ hypoplastic nipples, have occurred in infants born to mothers who received methimazole during pregnancy. If methimazole is used during pregnancy or if the patient becomes pregnant while taking this drug, the patient should be warned of the potential hazard to the fetus.

Since the above congenital defects have been reported in offspring of patients treated with methimazole, it may be appropriate to use other agents in pregnant women requiring treatment for hyperthyroidism.

Postpartum patients receiving methimazole should not nurse their babies.

PRECAUTIONS

General

Patients who receive methimazole should be under close surveillance and should be cautioned to report immediately any evidence of illness, particularly sore throat, skin eruptions, fever, headache, or general malaise. In such cases, white blood cell and differential counts should be made to determine whether agranulocytosis has developed. Particular care should be exercised with patients who are receiving additional drugs known to cause agranulocytosis.

Laboratory Tests

Because methimazole may cause hypoprothrombinemia and bleeding, prothrombin time should be monitored during therapy with the drug, especially before surgical procedures (see General under PRECAUTIONS).

Periodic monitoring of thyroid function is warranted, and the finding of an elevated TSH warrants a decrease in the dosage of methimazole.

Drug Interactions

Anticoagulants (oral) - The activity of oral anticoagulants may be potentiated by anti-vitamin-K activity attributed to methimazole.

β-adrenergic blocking agents – Hyperthyroidism may cause an increased clearance of beta blockers with a high extraction ratio. A dose reduction of beta-adrenergic blockers may be needed when a hyperthyroid patient becomes euthyroid.

Digitalis glycosides - Serum digitalis levels may be increased when hyperthyroid patients on a stable digitalis glycoside regimen become euthyroid; a reduced dosage of digitalis glycosides may be required.

Theophylline - Theophylline clearance may decrease when hyperthyroid patients on a stable theophylline regimen become euthyroid; a reduced dose of theophylline may be needed.

Carcinogenesis, Mutagenesis, Impairment of Fertility

In a 2 year study, rats were given methimazole at doses of 0.5, 3, and 18 mg/kg/day. These doses were 0.3, 2 and 12 times the 15 mg/ day maximum human maintenance dose (when calculated on the basis of surface area).

Thyroid hyperplasia, adenoma, and carcinoma developed in rats at the two higher doses. The clinical significance of these findings is unclear.

Pregnancy

Category D (See WARNINGS)

Methimazole used judiciously is an effective drug in hyperthyroidism complicated by pregnancy. In many pregnant women, the thyroid dysfunction diminishes as the pregnancy proceeds; consequently, a reduction in dosage may be possible. In some instances, use of methimazole can be discontinued 2 or 3 weeks before delivery.

Nursing Mothers

The drug appears in human breast milk and its use is contraindicated in nursing mothers (see WARNINGS).

Pediatric use

(See DOSAGE AND ADMINISTRATION).

ADVERSE REACTIONS

Major adverse reactions (which occur with much less frequency than the minor adverse reactions) include inhibition of myelopoiesis (agranulocytosis, granulocytopenia, and thrombocytopenia), aplastic anemia, drug fever, a lupus like syndrome, insulin autoimmune syndrome (which can result in hypoglycemic coma), hepatitis (jaundice may persist for several weeks after discontinuation of the drug), periarteritis, and hypoprothrombinemia. Nephritis occurs very rarely.

Minor adverse reactions include skin rash, urticaria, nausea, vomiting, epigastric distress, arthralgia, paresthesia, loss of taste, abnormal loss of hair, myalgia, headache, pruritus, drowsiness, neuritis, edema, vertigo, skin pigmentation, jaundice, sialadenopathy, and lymphadenopathy.

It should be noted that about 10% of patients with untreated hyperthyroidism have leukopenia (white blood cell count of less than 4,000/mm^3), often with relative granulopenia.

OVERDOSAGE

Signs and Symptoms

Symptoms may include nausea, vomiting, epigastric distress, headache, fever, joint pain, pruritus, and edema. Aplastic anemia (pancytopenia) or agranulocytosis may be manifested in hours to days. Less frequent events are hepatitis, nephrotic syndrome, exfoliative dermatitis, neuropathies, and CNS stimulation or depression. Although not well studied, methimazole-induced agranulocytosis is generally associated with doses of 40 mg or more in patients older than 40 years of age.

No information is available on the median lethal dose of the drug or the concentration of methimazole in biologic fluids associated with toxicity and/or death.

Treatment

To obtain up-to-date information about the treatment of overdose, a good resource is your certified Regional Poison Control Center.

Telephone numbers of certified poison control centers are listed in the “Physicians’ Desk Reference (PDR)”. In managing overdosage, consider the possibility of multiple drug overdoses, interaction among drugs, and unusual drug kinetics in your patient.

Protect the patient’s airway and support ventilation and perfusion. Meticulously monitor and maintain, within acceptable limits, the patient’s vital signs, blood gases, serum electrolytes, etc. The patient’s bone marrow function should be monitored. Absorption of drugs from the gastrointestinal tract may be decreased by giving activated charcoal, which, in many cases, is more effective than emesis or lavage; consider charcoal instead of or in addition to gastric emptying. Repeated doses of charcoal over time may hasten elimination of some drugs that have been absorbed. Safeguard the patient’s airway when employing gastric emptying or charcoal.

Forced diuresis, peritoneal dialysis, hemodialysis, or charcoal hemoperfusion have not been established as beneficial for an overdose of methimazole.

DOSAGE AND ADMINISTRATION

Methimazole is administered orally. It is usually given in 3 equal doses at approximately 8-hour intervals.

Adults

The initial daily dosage is 15 mg for mild hyperthyroidism, 30 to 40 mg for moderately severe hyperthyroidism, and 60 mg for severe hyperthyroidism, divided into 3 doses at 8-hour intervals. The maintenance dosage is 5 to 15 mg daily.

Pediatric

Initially, the daily dosage is 0.4 mg/kg of body weight divided into 3 doses and given at 8-hour intervals. The maintenance dosage is approximately 1/2 of the initial dose.

HOW SUPPLIED

Methimazole Tablets, USP 10 mg - white to off-white, round, biconvex tablets, with “B” to the left and “P” to right of the break line on one side and “656” on the other.

They are available in:

Bottle of 20 - 68788-0681-2

Bottle of 30 - 68788-0681-3

Bottle of 60 - 68788-0681-6

Bottle of 90 - 68788-0681-9

Bottle of 100 - 68788-0681-1

KEEP THIS AND ALL DRUGS OUT OF REACH OF CHILDREN.

Dispense in a tight, light-resistant container. Keep tightly closed.

STORAGE AND HANDLING

Store at controlled room temperature 15°–30°C (59°–86°F).

Manufactured for:
Boca Pharmacal, LLC
a Subsidiary of Qualitest Pharmaceuticals
Huntsville, AL 35811
1-800-444-4011

Iss. 12/14

QT-TED-655

Repackaged By: Preferred Pharmaceuticals Inc.